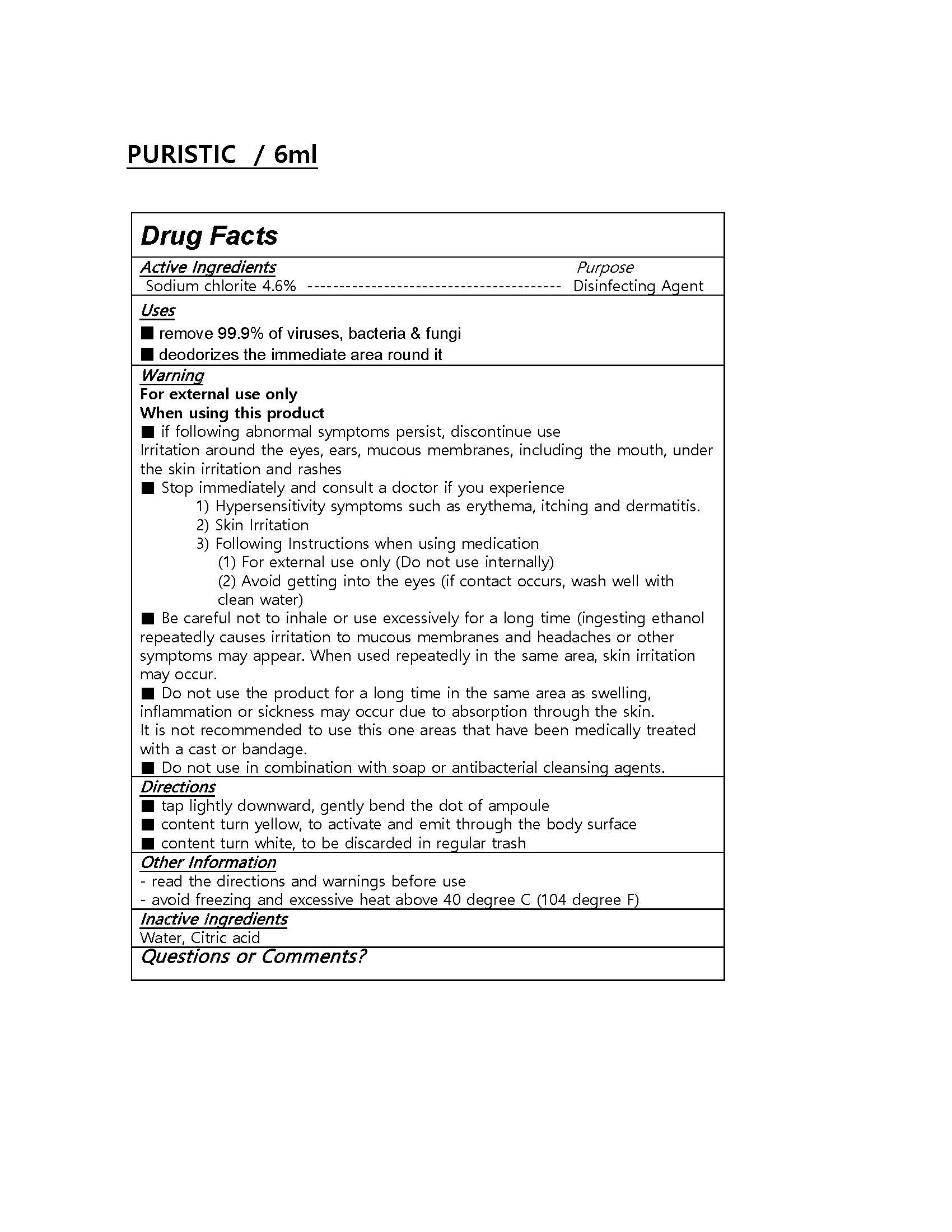 DRUG LABEL: PURISTIC
NDC: 76648-0001 | Form: LIQUID
Manufacturer: Purgofarm Co Ltd
Category: otc | Type: HUMAN OTC DRUG LABEL
Date: 20200425

ACTIVE INGREDIENTS: SODIUM CHLORITE 4.6 g/100 mL
INACTIVE INGREDIENTS: WATER; CITRIC ACID ACETATE

CT Cosmetics Co., Ltd - Hug Lets CC Hand Sanitizer Gel(Ethanol)

ACTIVE INGREDIENT

sodium chlorite

INACTIVE INGREDIENT

water, citric acid

PURPOSE

■ remove 99.9% of viruses, bacteria & fungi

■ deodorizes the immediate area round it

keep out of reach of the children

INDICATIONS AND USAGE

■ tap lightly downward, gently bend the dot of ampoule

■ content turn yellow, to activate and emit through the body surface

■ content turn white, to be discarded in regular trash

WARNINGS

For external use only. Flammable. Keep away from heat or flame.

Do not use

- in children less than 2 months of age
- on open skin wounds

When using this product keep out of eyes, ears, and mouth. In case of contact with eyes, rinse thoroughly with water.

Stop use and ask a doctor if irritation or rash occurs. These may be signs of a serious condition.

Keep out of reach of children. If swallowed, get medical help or contact a Poison Control Center right away.

DOSAGE AND ADMINISTRATION

for external use only